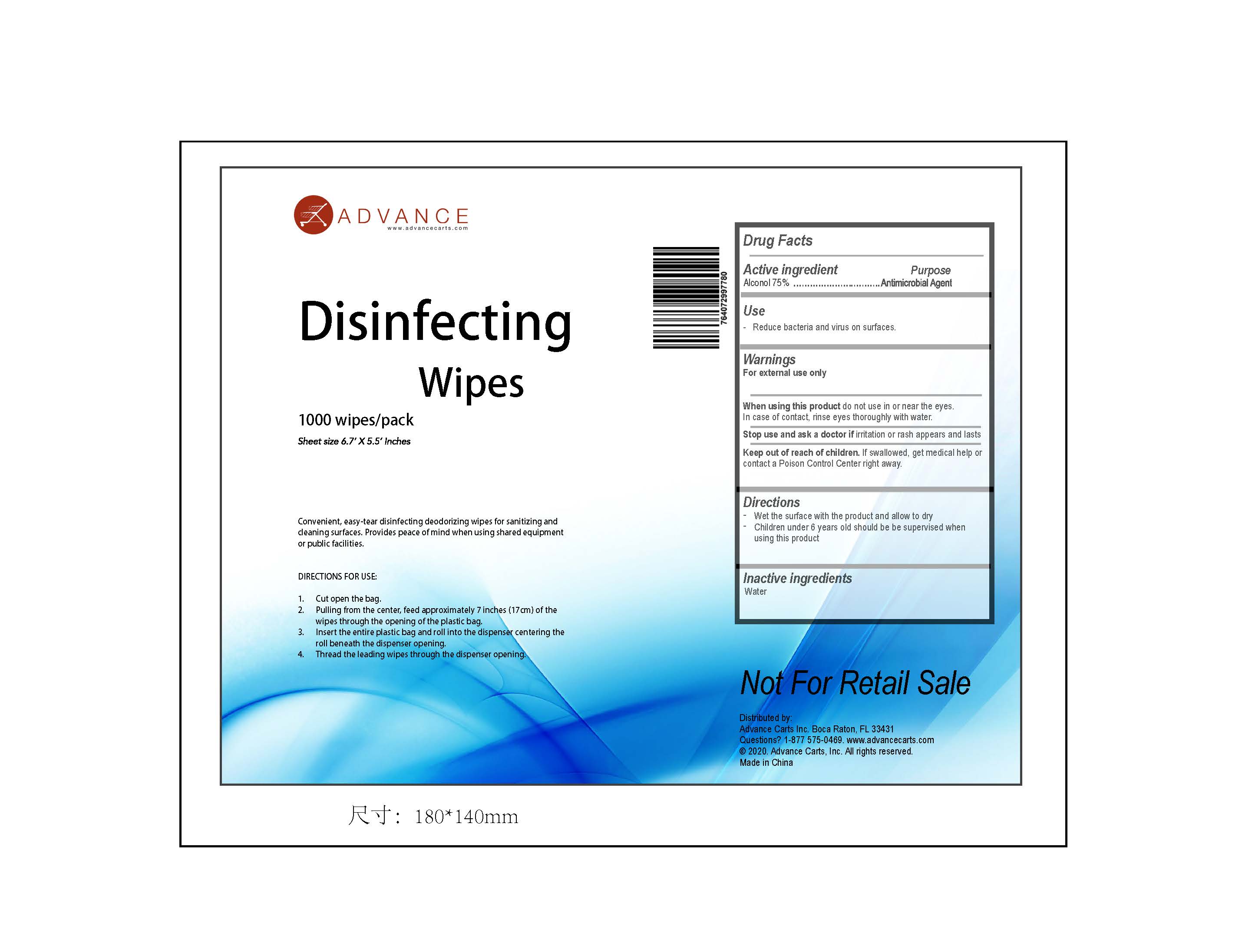 DRUG LABEL: Disinfecting Wipes
NDC: 76991-011 | Form: CLOTH
Manufacturer: Hefei Wenqi Industrial & Trade Co., Ltd
Category: otc | Type: HUMAN OTC DRUG LABEL
Date: 20200910

ACTIVE INGREDIENTS: ALCOHOL 75 mL/100 1
INACTIVE INGREDIENTS: WATER

76991-011
Disinfecting Wipes

Active Ingredient(s)

Alconol 75%

Purpose

Antimicrobial Agent

Use

Reduce bacteria and virus on surfaces.

Warnings

For external use only

When using this product do not use in or near the eyes.
In case of contact, rinse eyes thoroughly with water.

Stop use and ask a doctor if irritation or rash appears and lasts

Keep out of reach of children. If swallowed, get medical help or contact a Poison Control Center right away.

Do not use

/

When using this product do not use in or near the eyes.
In case of contact, rinse eyes thoroughly with water.

Stop use and ask a doctor if irritation or rash appears and lasts

Keep out of reach of children. If swallowed, get medical help or contact a Poison Control Center right away.

Stop use and ask a doctor if irritation or rash appears and lasts

Directions

- Wet the surface with the product and allow to dry
- Children under 6 years old should be be supervised when using this product

Other information

/

Inactive ingredients

water